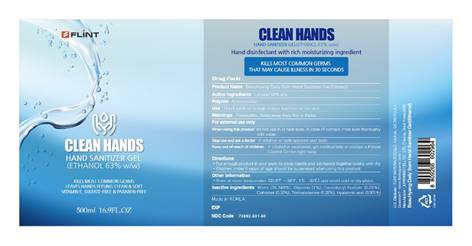 DRUG LABEL: BeauHyang Daily Sum Hand Sanitizer Gel
NDC: 73892-0003 | Form: GEL
Manufacturer: JUHWANBIO.CELL CO.,LTD.
Category: otc | Type: HUMAN OTC DRUG LABEL
Date: 20200403

ACTIVE INGREDIENTS: ALCOHOL 67.7 mL/100 mL
INACTIVE INGREDIENTS: WATER; GLYCERIN; .ALPHA.-TOCOPHEROL ACETATE; CARBOMER HOMOPOLYMER, UNSPECIFIED TYPE; TROLAMINE; HYALURONIC ACID

CLEAN HANDS HAND SANITIZER GEL

Active ingredients

Ethanol 67.7% (v/v)

Purpose

Antimicrobial

Use

Hand sanitizer to help reduce bacteria on the skin

Warnings

Flammable. Keep away from fire or flame.

For external use only

When using this product do not use in or near eyes. In case of contact, rinse eyes thoroughly with water.

Stop use and ask a doctor if irritation or rash appears and lasts

Keep out of reach of children. If inhaled or swallowed, get medical help or contact a Poison Control Center right away

Directions

• Put enough product in your palm to cover hands and rub hands together briskly until dry

• Children under 6 years of age should be supervised when using this product

Other information

• Store at room temperature (33.8°F - 86°F, 1°C - 30°C) and avoid cold or dry place.

Inactive ingredients

Water (30.879%), Glycerin (0.87%), Tocopheryl Acetate (0.01%), Carbomer (0.27%), Triethanolamine (0.27%), Hyaluronic acid (0.001%)

FLiNT

KILLS MORE THAN GERMS

LEAVES HANDS FEELING CLEAN & SOFT

VITAMIN E, SULFATE-FREE & PARABEN-FREE

Hand disinfectant with rich moisturizing ingredient

KILLS MOST COMMON GERMS THAT MAY CAUSE ILLNESS IN 30 SECONDS

Made in KOREA

U.S. Distributor: FLINT MATERIALS CO LLC., Cochran, GA 31014 U.S.A

Question? www.flinthygiene.com